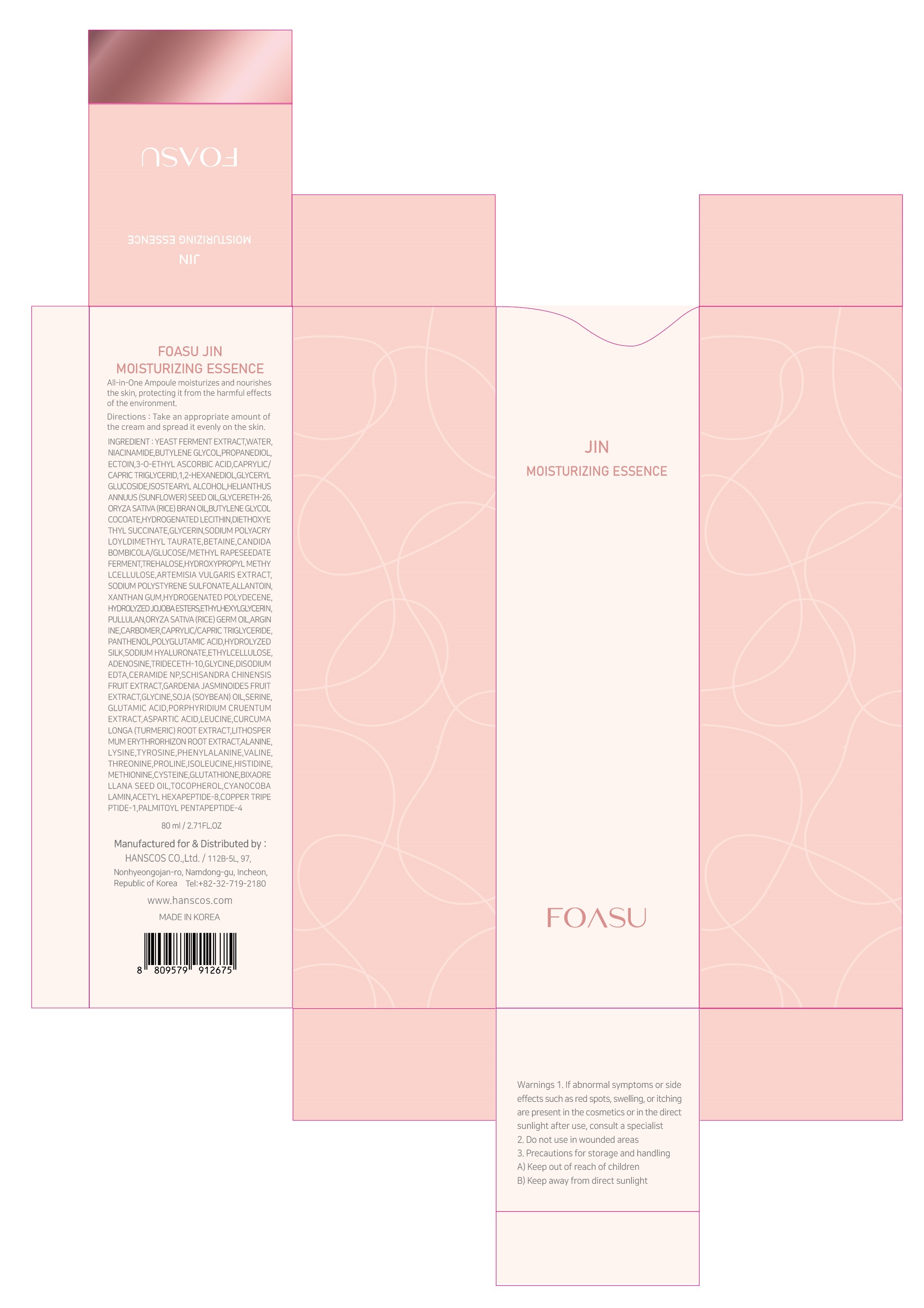 DRUG LABEL: FOASU JIN MOISTURIZING ESSENCE
NDC: 77964-003 | Form: LIQUID
Manufacturer: HANSCOS Co.,Ltd.
Category: otc | Type: HUMAN OTC DRUG LABEL
Date: 20220226

ACTIVE INGREDIENTS: ADENOSINE 0.04 g/100 mL; NIACINAMIDE 3 g/100 mL
INACTIVE INGREDIENTS: WATER; GLYCERIN

Active ingredient

niacinamide, adenosine

Purpose

skin protectant

Use

apply proper amount to the skin

Warnings

For external use only

1) Please consult your doctor if you experience side effects such as swelling, itching, or reddening on the area where you applied this product

2) Do not apply on wounds or cuts. 3) Do not store where children may reach, and avoid keeping it exposed to direct sunlight.

Directions

for external use only

Inactive ingredients

YEAST FERMENT EXTRACT
WATER
BUTYLENE GLYCOL
PROPANEDIOL
ECTOIN
3-O-ETHYL ASCORBIC ACID
CAPRYLIC/CAPRIC TRIGLYCERID
1,2-HEXANEDIOL
GLYCERYL GLUCOSIDE
ISOSTEARYL ALCOHOL
HELIANTHUS ANNUUS (SUNFLOWER) SEED OIL
GLYCERETH-26
ORYZA SATIVA (RICE) BRAN OIL
BUTYLENE GLYCOL COCOATE
HYDROGENATED LECITHIN
DIETHOXYETHYL SUCCINATE
GLYCERIN
SODIUM POLYACRYLOYLDIMETHYL TAURATE
BETAINE
CANDIDA BOMBICOLA/GLUCOSE/METHYL RAPESEEDATE FERMENT
TREHALOSE
HYDROXYPROPYL METHYLCELLULOSE
ARTEMISIA VULGARIS EXTRACT
SODIUM POLYSTYRENE SULFONATE
ALLANTOIN
XANTHAN GUM
HYDROGENATED POLYDECENE
HYDROLYZED JOJOBA ESTERS
ETHYLHEXYLGLYCERIN
PULLULAN
ORYZA SATIVA (RICE) GERM OIL
ARGININE
CARBOMER
CAPRYLIC/CAPRIC TRIGLYCERIDE
PANTHENOL
POLYGLUTAMIC ACID
HYDROLYZED SILK
SODIUM HYALURONATE
ETHYLCELLULOSE
TRIDECETH-10
GLYCINE
DISODIUM EDTA
CERAMIDE NP
SCHISANDRA CHINENSIS FRUIT EXTRACT
GARDENIA JASMINOIDES FRUIT EXTRACT
GLYCINE SOJA (SOYBEAN) OIL
SERINE
GLUTAMIC ACID
PORPHYRIDIUM CRUENTUM EXTRACT
ASPARTIC ACID
LEUCINE
CURCUMA LONGA (TURMERIC) ROOT EXTRACT
LITHOSPERMUM ERYTHRORHIZON ROOT EXTRACT
ALANINE
LYSINE
TYROSINE
PHENYLALANINE
VALINE
THREONINE
PROLINE
ISOLEUCINE
HISTIDINE
METHIONINE
CYSTEINE
GLUTATHIONE
BIXA ORELLANA SEED OIL
TOCOPHEROL
CYANOCOBALAMIN
ACETYL HEXAPEPTIDE-8
COPPER TRIPEPTIDE-1
PALMITOYL PENTAPEPTIDE-4

Keep out of reach of children. If swallowed, get medical help or contact a Poison Control Center right away.